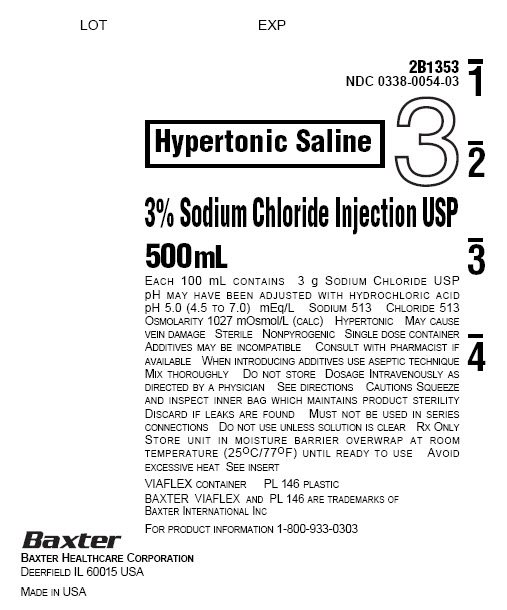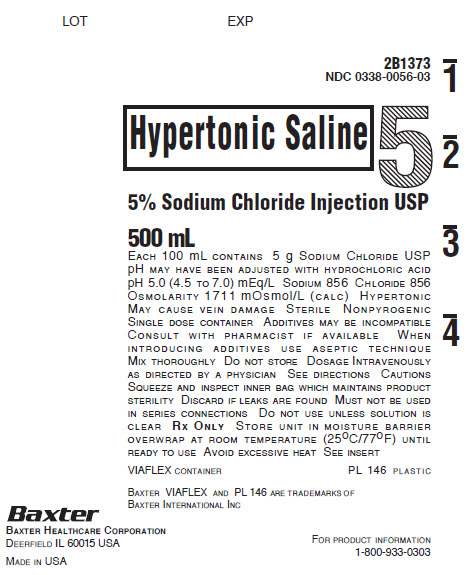 DRUG LABEL: Sodium Chloride
NDC: 0338-0054 | Form: INJECTION, SOLUTION
Manufacturer: Baxter Healthcare Corporation
Category: prescription | Type: HUMAN PRESCRIPTION DRUG LABEL
Date: 20180523

ACTIVE INGREDIENTS: SODIUM CHLORIDE 3 g/100 mL
INACTIVE INGREDIENTS: HYDROCHLORIC ACID; WATER

3% AND 5% SODIUM CHLORIDE INJECTION, USP
IN VIAFLEX PLASTIC CONTAINER

DESCRIPTION

3% and 5% Sodium Chloride Injection, USP is a sterile, nonpyrogenic, hypertonic solution for fluid and electrolyte replenishment in single dose containers for intravenous administration. The pH may have been adjusted with hydrochloric acid. It contains no antimicrobial agents. Composition, ionic concentration, osmolarity, and pH are shown in Table 1.

Table 1
 | size (mL) | Composition (g/L) | Ionic Concentration (mEq/L) |  | [Normal physiological osmolarity range is approximately 280 to 310 mOsmol/L.] Osmolarity (mOsmol/L) (calc) | pH
 | size (mL) | Sodium Chloride USP (NaCl) | Sodium | Chloride | [Normal physiological osmolarity range is approximately 280 to 310 mOsmol/L.] Osmolarity (mOsmol/L) (calc) | pH
3% Sodium Chloride Injection, USP | 500 | 30 | 513 | 513 | 1027 | 5.0 (4.5 to 7.0)
5% Sodium Chloride Injection, USP | 500 | 30 | 856 | 856 | 1711 | 5.0 (4.5 to 7.0)

The VIAFLEX plastic container is fabricated from a specially formulated polyvinyl chloride (PL 146 Plastic). The amount of water that can permeate from inside the container into the overwrap is insufficient to affect the solution significantly. Solutions in contact with the plastic container can leach out certain of its chemical components in very small amounts within the expiration period, e.g., di-2-ethylhexyl phthalate (DEHP), up to 5 parts per million. However, the safety of the plastic has been confirmed in tests in animals according to USP biological tests for plastic containers as well as by tissue culture toxicity studies.

CLINICAL PHARMACOLOGY

3% and 5% Sodium Chloride Injection, USP has value as a source of water and electrolytes. It is capable of inducing diuresis depending on the clinical condition of the patient.

INDICATIONS AND USAGE

3% and 5% Sodium Chloride Injection, USP is indicated as a source of water and electrolytes.

CONTRAINDICATIONS

None known.

WARNINGS

Hypersensitivity/infusion reactions, including hypotension, pyrexia, tremor, chills, urticaria, rash, and pruritus may occur with 3% and 5% Sodium Chloride Injection, USP.

Stop the infusion immediately if signs or symptoms of a hypersensitivity reaction develop, such as tachycardia, chest pain, dyspnea and flushing. Appropriate therapeutic countermeasures must be instituted as clinically indicated.

Depending on the volume and rate of infusion, the intravenous administration of 3% and 5% Sodium Chloride Injection, USP can cause fluid and/or solute overloading resulting in dilution of serum electrolyte concentrations, overhydration/hypervolemia, congested states, pulmonary edema, or acid-base imbalance. The risk of dilutive states is inversely proportional to the electrolyte concentration of the injection. The risk of solute overload causing congested states with peripheral and pulmonary edema is directly proportional to the electrolyte concentrations of the injection.

Monitor changes in fluid balance, electrolyte concentrations, and acid base balance during prolonged parenteral therapy or whenever the condition of the patient or the rate of administration warrants such evaluation.

Administer 3% and 5% Sodium Chloride Injection, USP with particular caution to patients with or at risk for hypernatremia, hyperchloremia, hypervolemia or with conditions that may cause sodium retention, fluid overload and edema; such as patients with primary hyperaldosteronism, or secondary hyperaldosteronism (for example, associated with hypertension, congestive heart failure, liver disease (including cirrhosis), renal disease (including renal artery stenosis, nephrosclerosis) or pre-eclampsia). Certain medications may increase risk of sodium and fluid retention, see DRUG INTERACTIONS.

Administer 3% and 5% Sodium Chloride Injection, USP with particular caution to patients with severe renal impairment. In such patients administration of Sodium Chloride Injection, USP may result in sodium retention.

PRECAUTIONS

General

Do not connect flexible plastic containers in series in order to avoid air embolism due to possible residual air contained in the primary container. Such use could result in air embolism due to residual air being drawn from the primary container before administration of the fluid from the secondary container is completed.

Pressurizing intravenous solutions contained in flexible plastic containers to increase flow rates can result in air embolism if the residual air in the container is not fully evacuated prior to administration.

Use of a vented intravenous administration set with the vent in the open position could result in air embolism. Vented intravenous administration sets with the vent in the open position should not be used with flexible plastic containers.

3% and 5% Sodium Chloride Injection, USP is hypertonic with an osmolarity of 1027 mOsmol/L and 1711 mOsmol/L, respectively. Administration of hypertonic solutions may cause venous damage and thus should be administered through a large vein, for rapid dilution.

Do not mix or administer 3% and 5% Sodium Chloride Injection, USP solutions through the same administration set with whole blood or cellular blood components.

Rapid correction of hypo- and hypernatremia is potentially dangerous (risk of serious neurologic complications). Dosage, rate, and duration of administration should be determined by a physician experienced in intravenous fluid therapy.

Drug Interactions

Caution must be exercised in the administration of 3% and 5% Sodium Chloride Injection, USP to patients treated with drugs that may increase the risk of sodium and fluid retention, such as corticosteroids.

Caution is advised in patients treated with lithium. Renal sodium and lithium clearance may be increased during the administration of 3% and 5% Sodium Chloride Injection, USP. Administration of 3% and 5% Sodium Chloride Injection, USP may, therefore, result in decreased lithium levels.

Pregnancy

There are no adequate and well controlled studies with 3% and 5% Sodium Chloride Injection, USP in pregnant women and animal reproduction studies have not been conducted with this drug. Therefore, it is not known whether 3% and 5% Sodium Chloride Injection, USP can cause fetal harm when administered to a pregnant woman. 3% and 5% Sodium Chloride Injection, USP should be given during pregnancy only if the potential benefit justifies the potential risks to the fetus.

Nursing Mothers

It is not known whether this drug is excreted present in human milk. Because many drugs are excreted present in human milk, caution should be exercised when 3% and 5% Sodium Chloride Injection, USP is administered to a nursing woman.

Pediatric Use

The use of 3% and 5% Sodium Chloride Injection, USP in pediatric patients is based on clinical practice. (See DOSAGE AND ADMINISTRATION)

Plasma electrolyte concentrations should be closely monitored in the pediatric population as this population may have impaired ability to regulate fluids and electrolytes.

Geriatric Use

Clinical studies of 3% and 5% Sodium Chloride Injection, USP, did not include sufficient numbers of subjects aged 65 and over to determine whether they respond differently from younger subjects. Other reported clinical experience has not identified differences in responses between the elderly and younger patients. In general, dose selection for an elderly patient should be cautious, usually starting at the low end of the dosing range, reflecting the greater frequency of decreased hepatic, renal, or cardiac function, and of concomitant disease or other drug therapy.

This drug is known to be substantially excreted by the kidney, and the risk of toxic reactions to this drug may be greater in patients with impaired renal function. Because elderly patients are more likely to have decreased renal function, care should be taken in dose selection, and it may be useful to monitor renal function.

ADVERSE REACTIONS

Post-Marketing Adverse Reactions

The following adverse reactions have not been reported with 3% and 5% Sodium Chloride Injection, USP but may occur:

- hyperchloremia
- hyperchloremic metabolic acidosis,
- hypersensitivity/infusion reactions, including hypotension, pyrexia, tremor, chills, urticaria, rash, and pruritus,
- Infusion site reactions, such as thrombosis, phlebitis, irritation, infusion site erythema, injection site streaking, burning sensation, infusion site urticaria.

If an adverse reaction does occur, discontinue the infusion, evaluate the patient, institute appropriate therapeutic countermeasures, and save the remainder of the fluid for examination if deemed necessary.

OVERDOSAGE

Excessive administration of 3% and 5% Sodium Chloride Injection, USP may lead to hypernatremia (which can lead to CNS manifestations, including seizures, coma, cerebral edema and death) and sodium overload (which can lead to central and/or peripheral edema).

When assessing an overdose, any additives in the solution must also be considered. The effects of an overdose may require immediate medical attention and treatment.

DOSAGE AND ADMINISTRATION

As directed by a physician. Dosage, rate, and duration of administration are to be individualized and depend upon the indication for use, the patient’s age, weight, clinical condition, concomitant treatment, and on the patient’s clinical and laboratory response to treatment.

Parenteral drug products should be inspected visually for particulate matter and discoloration prior to administration whenever solution and container permit. Use of a final filter is recommended during administration of all parenteral solutions, where possible.

Do not administer unless solution is clear and seal is intact.

All injections in VIAFLEX plastic containers are intended for intravenous administration using sterile and nonpyrogenic equipment.

Additives may be incompatible. Complete information is not available. Those additives known to be incompatible should not be used. Consult with pharmacist, if available. If, in the informed judgment of the physician, it is deemed advisable to introduce additives, use aseptic technique. Mix thoroughly when additives have been introduced. Do not store solutions containing additives.

After opening the container, the contents should be used immediately and should not be stored for a subsequent infusion. Do not reconnect any partially used containers. Discard any unused portion.

HOW SUPPLIED

3% and 5% Sodium Chloride Injection, USP in VIAFLEX plastic container is available as follows:

Code | Size (mL) | NDC | Product Name
2B1353 | 500 | 0338-0054-03 | 3% Sodium Chloride Injection, USP
2B1373 | 500 | 0338-0056-03 | 5% Sodium Chloride Injection, USP

Exposure of pharmaceutical products to heat should be minimized. Avoid excessive heat. It is recommended the product be stored at room temperature (25°C/77°F); brief exposure up to 40°C /104°F does not adversely affect the product.

DIRECTIONS FOR USE OF VIAFLEX PLASTIC CONTAINER

For Information on Risk of Air Embolism – see PRECAUTIONS.

To Open

Tear overwrap down side at slit and remove solution container. Visually inspect the container. If the outlet port protector is damaged, detached, or not present, discard container as solution path sterility may be impaired. Some opacity of the plastic due to moisture absorption during the sterilization process may be observed. This is normal and does not affect the solution quality or safety. The opacity will diminish gradually. Check for minute leaks by squeezing inner bag firmly. If leaks are found, discard solution as sterility may be impaired. If supplemental medication is desired, follow directions below.

Preparation for Administration

1. Suspend container from eyelet support.
2. Remove protector from outlet port at bottom of container.
3. Attach administration set. Refer to complete directions accompanying set.

To Add Medication

Warning: Additives may be incompatible - see DOSAGE AND ADMINISTRATION.

To add medication before solution administration

1. Prepare medication site.
2. Using syringe with 19 to 22 gauge needle, puncture resealable medication port and inject.
3. Mix solution and medication thoroughly. For high density medication such as potassium chloride, squeeze ports while ports are upright and mix thoroughly.

To add medication during solution administration

1. Close clamp on the set.
2. Prepare medication site.
3. Using syringe with 19 to 22 gauge needle, puncture resealable medication port and inject.
4. Remove container from IV pole and/or turn to an upright position.
5. Evacuate both ports by squeezing them while container is in the upright position.
6. Mix solution and medication thoroughly.
7. Return container to in use position and continue administration.

Baxter Healthcare Corporation
Deerfield, IL 60015 USA
Printed in USA

07-19-00-0269

Rev. May 2018

Baxter and Viaflex are trademarks of Baxter International Inc.

PACKAGE LABEL - PRINCIPAL DISPLAY PANEL

LOT

EXP

2B1353

NDC 0338-0054-03

Hypertonic Saline

3% Sodium Chloride Injection USP

500mL

EACH 100 mL CONTAINS 3 g SODIUM CHLORIDE USP
pH MAY HAVE BEEN ADJUSTED WITH HYDROCHLORIC ACID
pH 5.0 (4.5 TO 7.0) mEq/L SODIUM 513 CHLORIDE 513
OSMOLARITY 1027 mOsmol/L (CALC) HYPERTONIC MAY CAUSE
VEIN DAMAGE STERILE NONPYROGENIC SINGLE DOSE CONTAINER
ADDITIVES MAY BE INCOMPATIBLE CONSULT WITH PHARMACIST IF
AVAILABLE WHEN INTRODUCING ADDITIVES USE ASEPTIC TECHNIQUE
MIX THOROUGHLY DO NOT STORE DOSAGE INTRAVENOUSLY AS
DIRECTED BY A PHYSICIAN SEE DIRECTIONS CAUTIONS SQUEEZE
AND INSPECT INNER BAG WHICH MAINTAINS PRODUCT STERILITY
DISCARD IF LEAKS ARE FOUND MUST NOT BE USED IN SERIES
CONNECTIONS DO NOT USE UNLESS SOLUTION IS CLEAR RX ONLY
STORE UNIT IN MOISTURE BARRIER OVERWRAP AT ROOM
TEMPERATURE (25°C/77°F) UNTIL READY TO USE AVOID
EXCESSIVE HEAT SEE INSERT

VIAFLEX CONTAINER

PL 146 PLASTIC

BAXTER VIAFLEX AND PL 146 ARE TRADEMARKS OF
BAXTER INTERNATIONAL INC

FOR PRODUCT INFORMATION 1-800-933-0303

Baxter Logo
BAXTER HEALTHCARE CORPORATION
DEERFIELD IL 60015 USA

MADE IN USA

LOT

EXP

2B1373

NDC 0338-0056-03

Hypertonic Saline

5% Sodium Chloride Injection USP

500mL

EACH 100 mL CONTAINS 5 g SODIUM CHLORIDE USP
pH MAY HAVE BEEN ADJUSTED WITH HYDROCHLORIC ACID
pH 5.0 (4.5 TO 7.0) mEq/L SODIUM 856 CHLORIDE 856
OSMOLARITY 1711 mOsmol/L (CALC) HYPERTONIC
MAY CAUSE VEIN DAMAGE STERILE NONPYROGENIC
SINGLE DOSE CONTAINER ADDITIVES MAY BE INCOMPATIBLE
CONSULT WITH PHARMACIST IF AVAILABLE WHEN
INTRODUCING ADDITIVES USE ASEPTIC TECHNIQUE
MIX THOROUGHLY DO NOT STORE DOSAGE INTRAVENOUSLY
AS DIRECTED BY A PHYSICIAN SEE DIRECTIONS CAUTIONS
SQUEEZE AND INSPECT INNER BAG WHICH MAINTAINS PRODUCT
STERILITY DISCARD IF LEAKS ARE FOUND MUST NOT BE USED
IN SERIES CONNECTIONS DO NOT USE UNLESS SOLUTION IS
CLEAR RX ONLY STORE UNIT IN MOISTURE BARRIER
OVERWRAP AT ROOM TEMPERATURE (25°C/77°F) UNTIL
READY TO USE AVOID EXCESSIVE HEAT SEE INSERT

VIAFLEX CONTAINER

PL 146 PLASTIC

BAXTER VIAFLEX AND PL 146 ARE TRADEMARKS OF
BAXTER INTERNATIONAL INC

FOR PRODUCT INFORMATION 1-800-933-0303

Baxter Logo
BAXTER HEALTHCARE CORPORATION
DEERFIELD IL 60015 USA

MADE IN USA